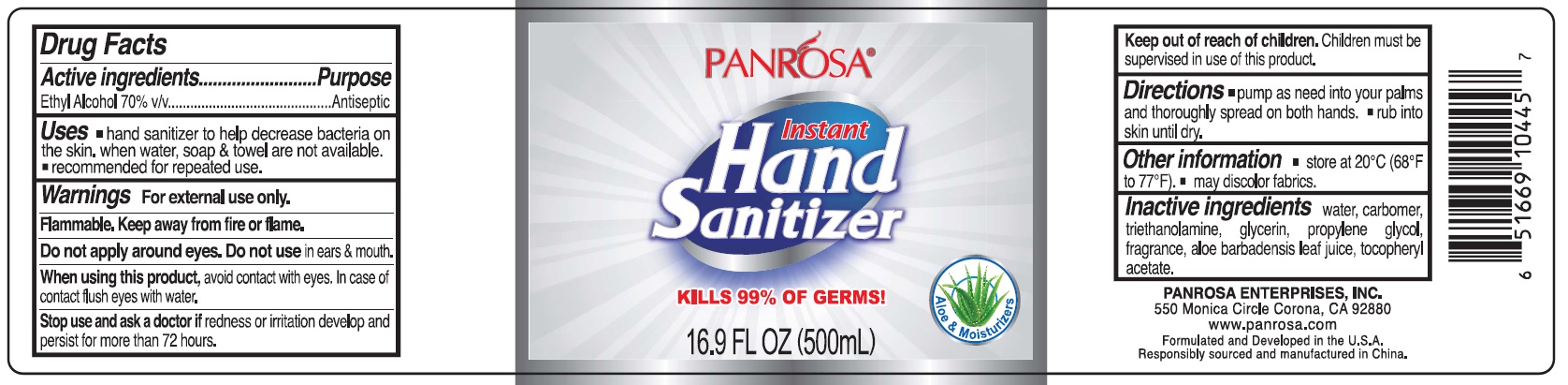 DRUG LABEL: Panrosa Instant Hand Sanitizer Clear
NDC: 50302-021 | Form: GEL
Manufacturer: Panrosa Enterprises, Inc.
Category: otc | Type: HUMAN OTC DRUG LABEL
Date: 20211020

ACTIVE INGREDIENTS: ALCOHOL 0.7 mL/1 mL
INACTIVE INGREDIENTS: WATER; CARBOMER HOMOPOLYMER, UNSPECIFIED TYPE; TROLAMINE; GLYCERIN; PROPYLENE GLYCOL; ALOE VERA LEAF; .ALPHA.-TOCOPHEROL ACETATE

Panrosa Instant Hand Sanitizer - Clear

Active ingredients

Ethyl Alcohol 70% v/v

Purpose

Antiseptic

Uses

- hand sanitizer to help decrease bacteria on the skin. when water, soap & towel are not available.
- recommended for repeated use.

Warnigns

For external use only.

Flammable. Keep away from fire or flame.

Do not apply around eyes.

Do not use

in ears & mouth.

When using this product,

avoid contact with eyes. In case of contact flush eyes with water.

Stop use and ask a doctor if

redness or irritation develop and persist for more than 72 hours.

Keep out of reach of children.

Children must be supervised in use of this product.

Directions

- pump as need into your palms and thoroughly spread on both hands.
- rub into skin until dry.

Other information

- store at 20°C (68°F to 77°F).
- may discolor fabrics.

Inactive ingredients

Water, carbomer, triethanolamine, glycerin, propylene glycol, fragrance, aloe barbadensis leaf juice, tocopheryl acetate.